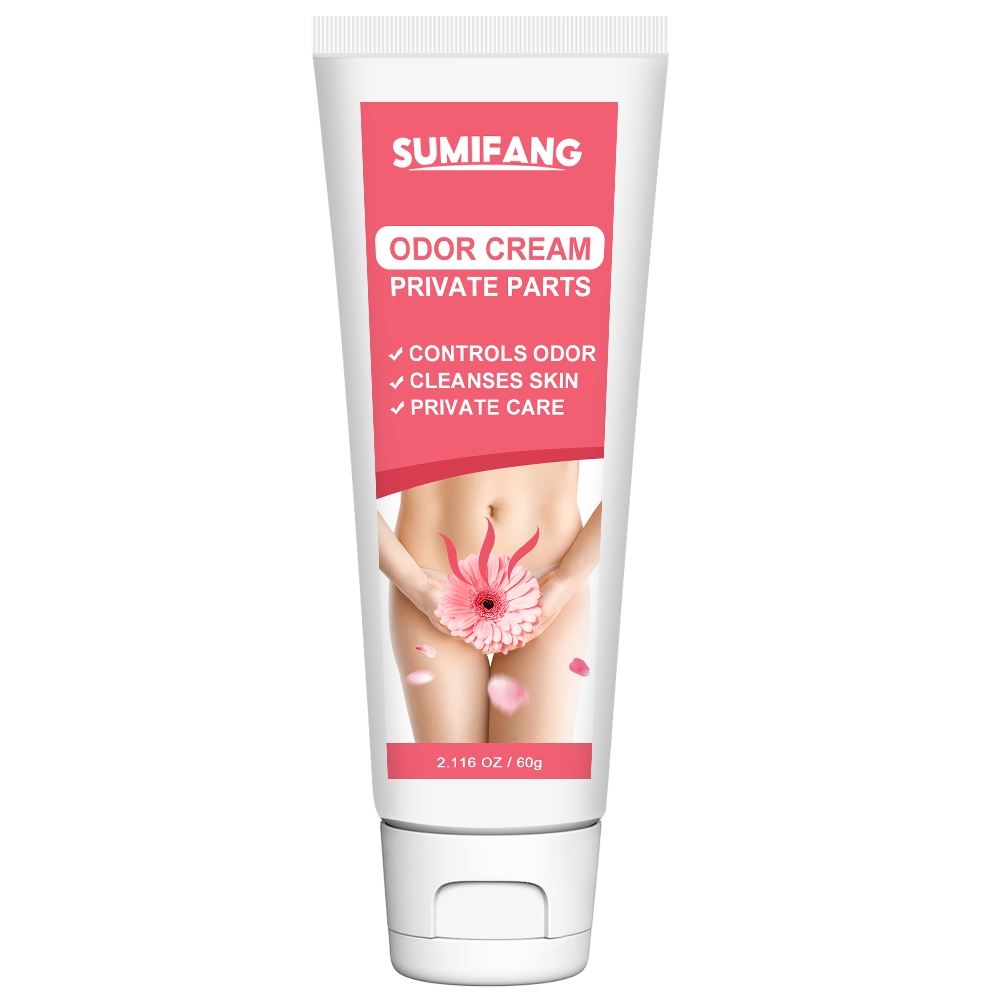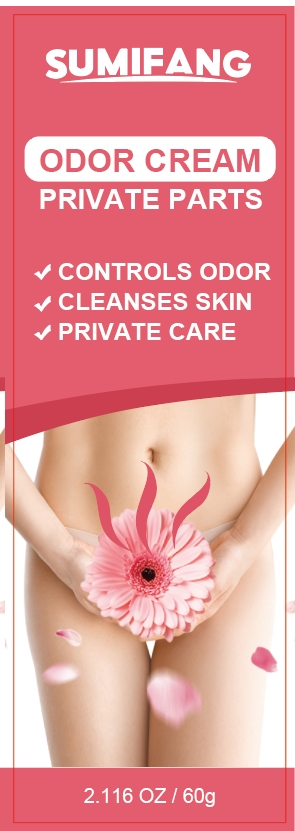 DRUG LABEL: ODOR CREAMPRIVATEPARTS
NDC: 84025-144 | Form: CREAM
Manufacturer: Guangzhou Yanxi Biotechnology Co.. Ltd
Category: otc | Type: HUMAN OTC DRUG LABEL
Date: 20240814

ACTIVE INGREDIENTS: GLYCERIN 3 mg/60 g; HYALURONIC ACID 5 mg/60 g
INACTIVE INGREDIENTS: WATER

DOSAGE AND ADMINISTRATION

For cleaning and care of private skin

WARNINGS

Keep out of children

INACTIVE INGREDIENT

Aqua

INDICATIONS AND USAGE

For the care of sensitive private skin

Keep out of children

PURPOSE

Reduce private skin odor and keep private skin healthy